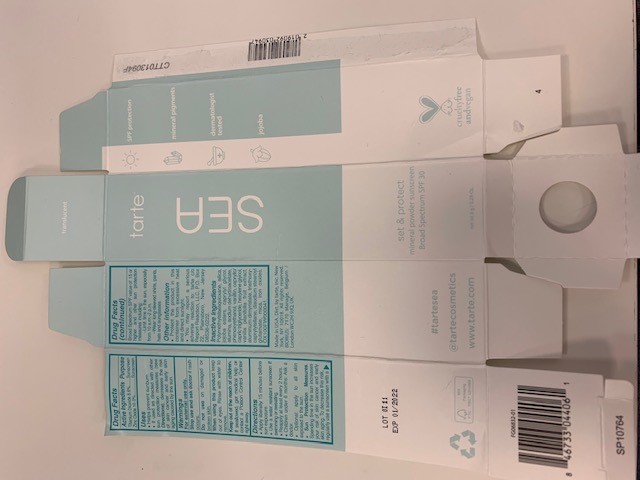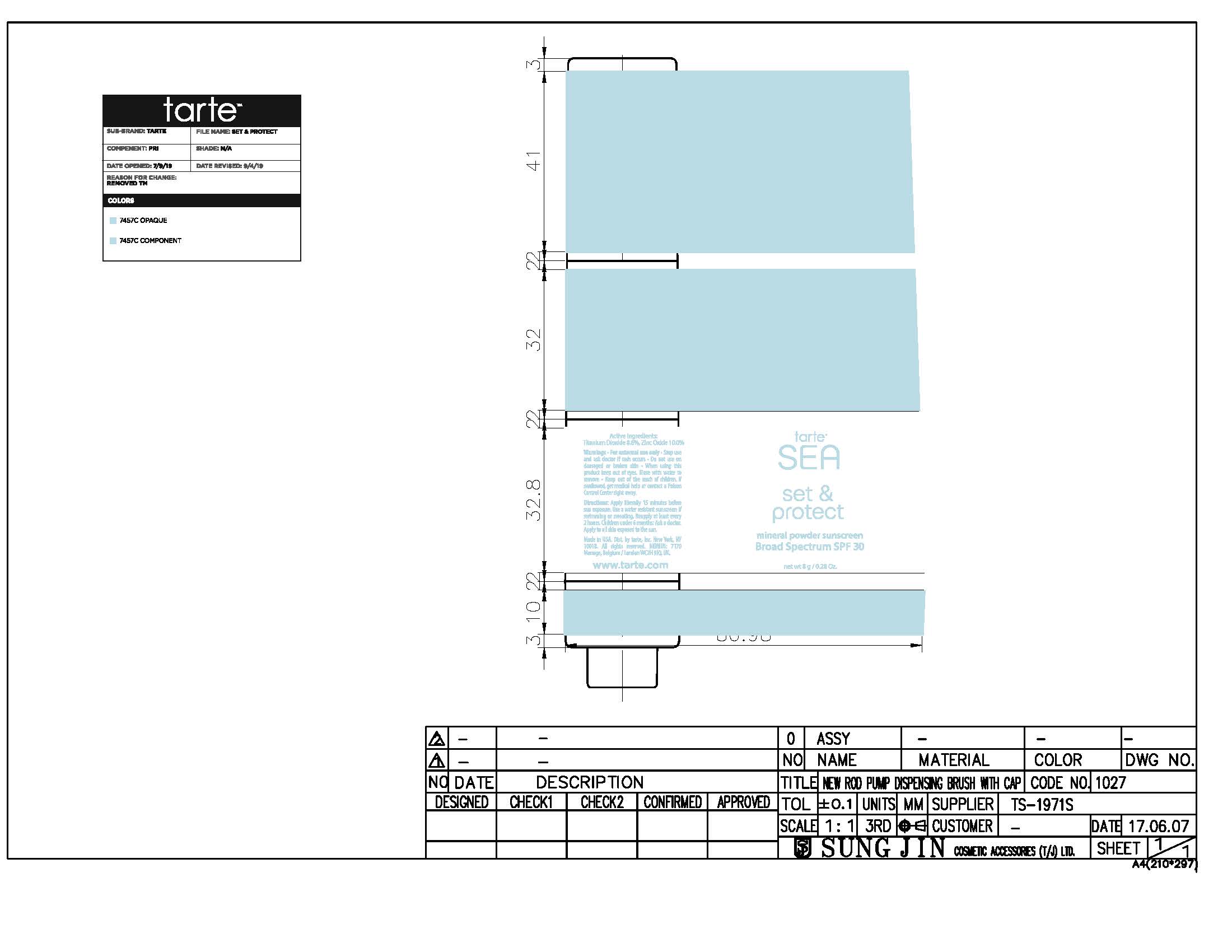 DRUG LABEL: powder
NDC: 61354-052 | Form: POWDER
Manufacturer: Oxygen development
Category: otc | Type: HUMAN OTC DRUG LABEL
Date: 20230210

ACTIVE INGREDIENTS: TITANIUM DIOXIDE 8.6 mg/100 mg; ZINC OXIDE 10 mg/100 mg
INACTIVE INGREDIENTS: JOJOBA OIL; POLYMETHYLSILSESQUIOXANE (4.5 MICRONS); SILICON DIOXIDE

SEA SET & PROTECT MINERAL POWDER SUNSCREEN BROAD SPECTRUM SPF 30 TRANSLUCENT

Active ingredients

Titanium Dioxide 8.6%

Zinc Oxide 10.0%

Purpose

Sunscreen

Uses

- Helps prevent sunburn.
- If used as directed with other sun protection measures (see Directions), decreases the risk of skin cancer and early skin again caused by the sun.

Warnings

For external use only

Stop Use

Stop use and ask doctor if rash occurs

Do not use on damaged or broken skin

When using

When using this product keep out of eyes. Rinse with water to remove

Keep out of the reach of children. If swallowed, get medical help or contact a Poison Control center rigth away

Directions

- Apply liberally 15 minutes before sun exposure.
- Use a water resistant sunscreen if swimming or sweating.
- Reapply at lease every 2 hours.
- Children under 6 months: ask a doctor.
- Optional: apply to all skin exposed to the sun.
- Sun Protection measures. Spending time in the sin increases your risk ofg skin cancer and early skin aging. To decrease this risk, regularly use a sunscreen with a broad spectrum SPF value of 15 or higher and other sun protection measures including: - limit time in the sun, especially from 10 a.m-2p.m. - Wear long-sleeved shirts, pants, hats and sunglasses.

Other information

- Protect the product in this container from excessive heat and direct sunlight.
- You may report a serious adverse reaction to: tarte c/o report Reaction, LLC,P.O.Box 22, Plainsboro, New Jersey 08536-0222.

Inactive Ingredients

Polymethylsilsesquioxane, silica, jojoba esters, caprylyl glycol, alumina, sodium dehydroacetate, phenoxyethanol, vanillin, caprylic/capric triglyceride, hexylene glycol, vanilla planifolia fruit extract, aluminum dimyristate, triethoxycaprylylsilane, disodium stearoyl glutamate, mica, iron oxides. OX100FW000041.

Primary package

8g 61354-052-02

Secondary Package

8g 61354-052-02